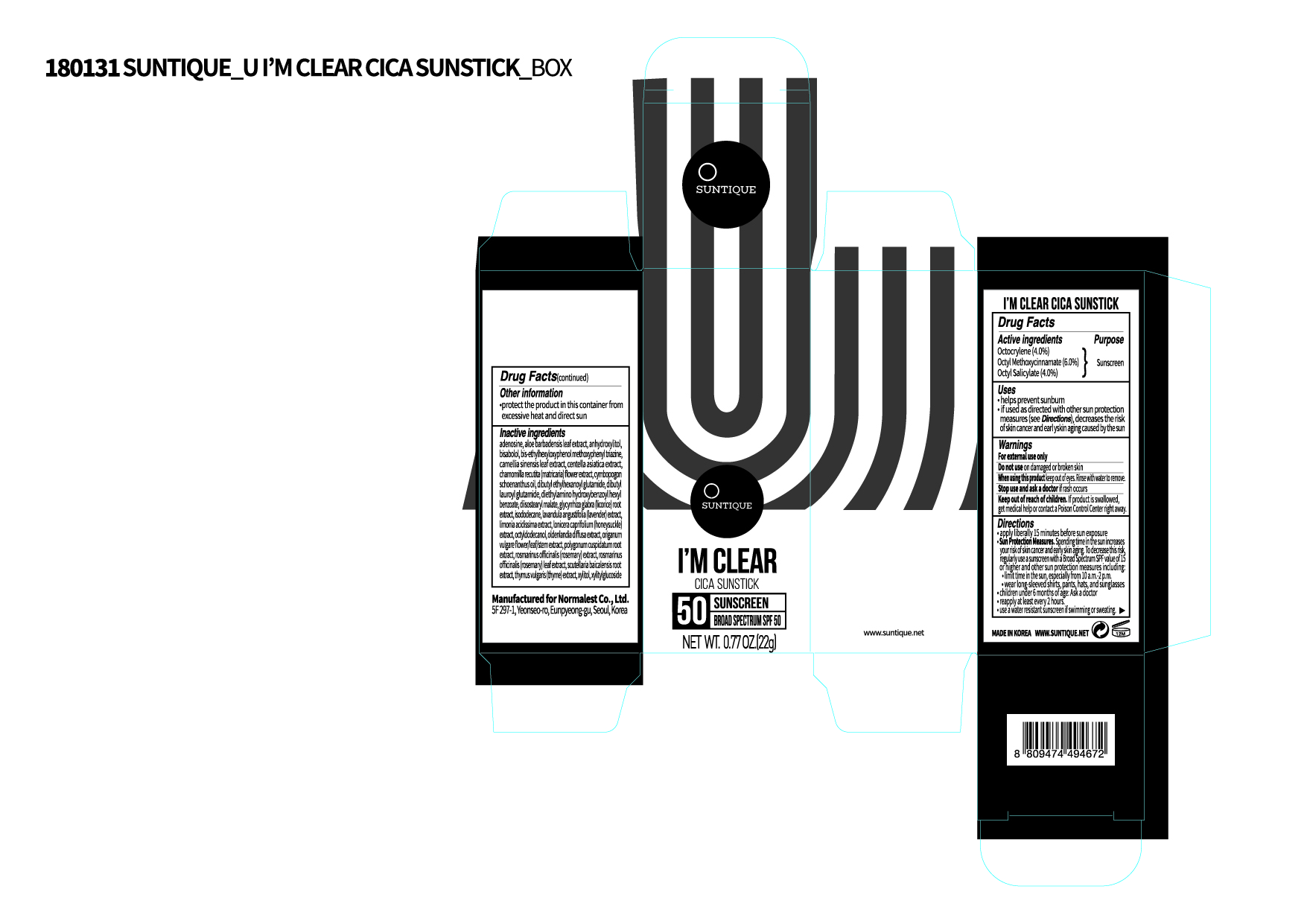 DRUG LABEL: IM CLEAR CICA SUNSTICK
NDC: 72284-0002 | Form: LOTION
Manufacturer: Normalest Co., Ltd.
Category: otc | Type: HUMAN OTC DRUG LABEL
Date: 20190305

ACTIVE INGREDIENTS: OCTOCRYLENE 0.88 g/22 g; OCTISALATE 0.88 g/22 g; OCTINOXATE 1.32 g/22 g
INACTIVE INGREDIENTS: DIBUTYL LAUROYL GLUTAMIDE; DIETHYLAMINO HYDROXYBENZOYL HEXYL BENZOATE; BEMOTRIZINOL; ALOE VERA LEAF; XYLITOL; LIMONIA ACIDISSIMA WOOD; BAMBUSA VULGARIS LEAF; LAVANDULA ANGUSTIFOLIA WHOLE; MATRICARIA CHAMOMILLA FLOWERING TOP; LONICERA CAPRIFOLIUM WHOLE; ORIGANUM VULGARE SUBSP. HIRTUM WHOLE; THYMUS VULGARIS WHOLE; GREEN TEA LEAF; SCUTELLARIA BAICALENSIS ROOT; ROSMARINUS OFFICINALIS WHOLE; CENTELLA ASIATICA; POLYGONUM CUSPIDATUM ROOT; CYMBOPOGON SCHOENANTHUS OIL; ADENOSINE; XYLITYLGLUCOSIDE; ISODODECANE; DIISOSTEARYL MALATE; DIBUTYL ETHYLHEXANOYL GLUTAMIDE; OCTYLDODECANOL; LEVOMENOL; ANHYDROXYLITOL; OLDENLANDIA DIFFUSA; GLYCYRRHIZA GLABRA

PACKAGE LABEL

Active ingredients

Octyl Methoxycinnamate 6%
Octyl Salicylate 4%
Octocrylene 4%

Inactive ingredients

Octyldodecanol, Isododecane, Diisostearyl Malate, Dibutyl Lauroyl Glutamide, Diethylamino Hydroxybenzoyl Hexyl Benzoate, Dibutyl Ethylhexanoyl Glutamide, Bis-Ethylhexyloxyphenol Methoxyphenyl Triazine, (-)-alpha-bisabolol, Cymbopogon Schoenanthus Oil, Adenosine, Aloe Barbadensis Leaf Extract, Xylitylglucoside, Anhydroxylitol, Xylitol, Limonia Acidissima Extract, Bambusa Vulgaris Leaf Extract, Oldenlandia Diffusa Extract, Lonicera Caprifolium (Honeysuckle) Extract, Lavandula Angustifolia (Lavender) Extract, Rosmarinus Officinalis (Rosemary) Extract, Origanum Vulgare Flower/Leaf/Stem Extract, Thymus Vulgaris (Thyme) Extract, Centella Asiatica Extract, Chamomilla Recutita (Matricaria) Flower Extract, Glycyrrhiza Glabra (Licorice) Root Extract, Camellia Sinensis Leaf Extract, Polygonum Cuspidatum Root Extract, Rosmarinus Officinalis (Rosemary) Leaf Extract, Scutellaria Baicalensis Root Extract